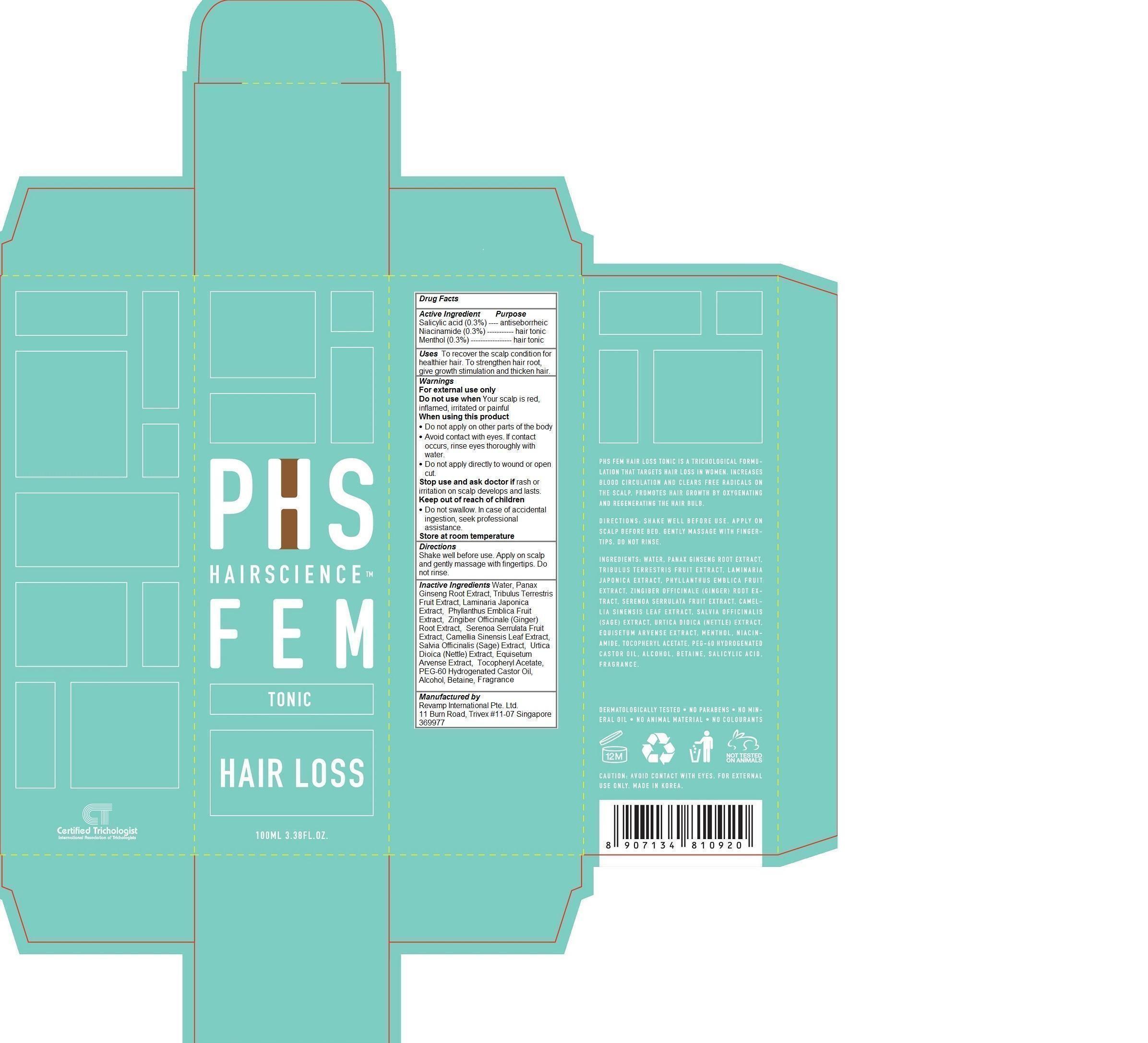 DRUG LABEL: PHS Hair Science Fem Hair Loss Tonic
NDC: 69149-101 | Form: LIQUID
Manufacturer: Revamp International Pte. Ltd.
Category: otc | Type: HUMAN OTC DRUG LABEL
Date: 20140919

ACTIVE INGREDIENTS: SALICYLIC ACID 0.3 1/100 mL; NIACINAMIDE 0.3 1/100 mL; MENTHOL 0.3 1/100 mL
INACTIVE INGREDIENTS: WATER; ASIAN GINSENG; TRIBULUS TERRESTRIS FRUIT; LAMINARIA JAPONICA; PHYLLANTHUS EMBLICA FRUIT; GINGER; SAW PALMETTO; GREEN TEA LEAF; SALVIA OFFICINALIS WHOLE; URTICA DIOICA LEAF; EQUISETUM ARVENSE BRANCH; .ALPHA.-TOCOPHEROL ACETATE; PEG-60 HYDROGENATED CASTOR OIL; ALCOHOL; BETAINE

PHS Hair Science Fem Hair Loss Tonic